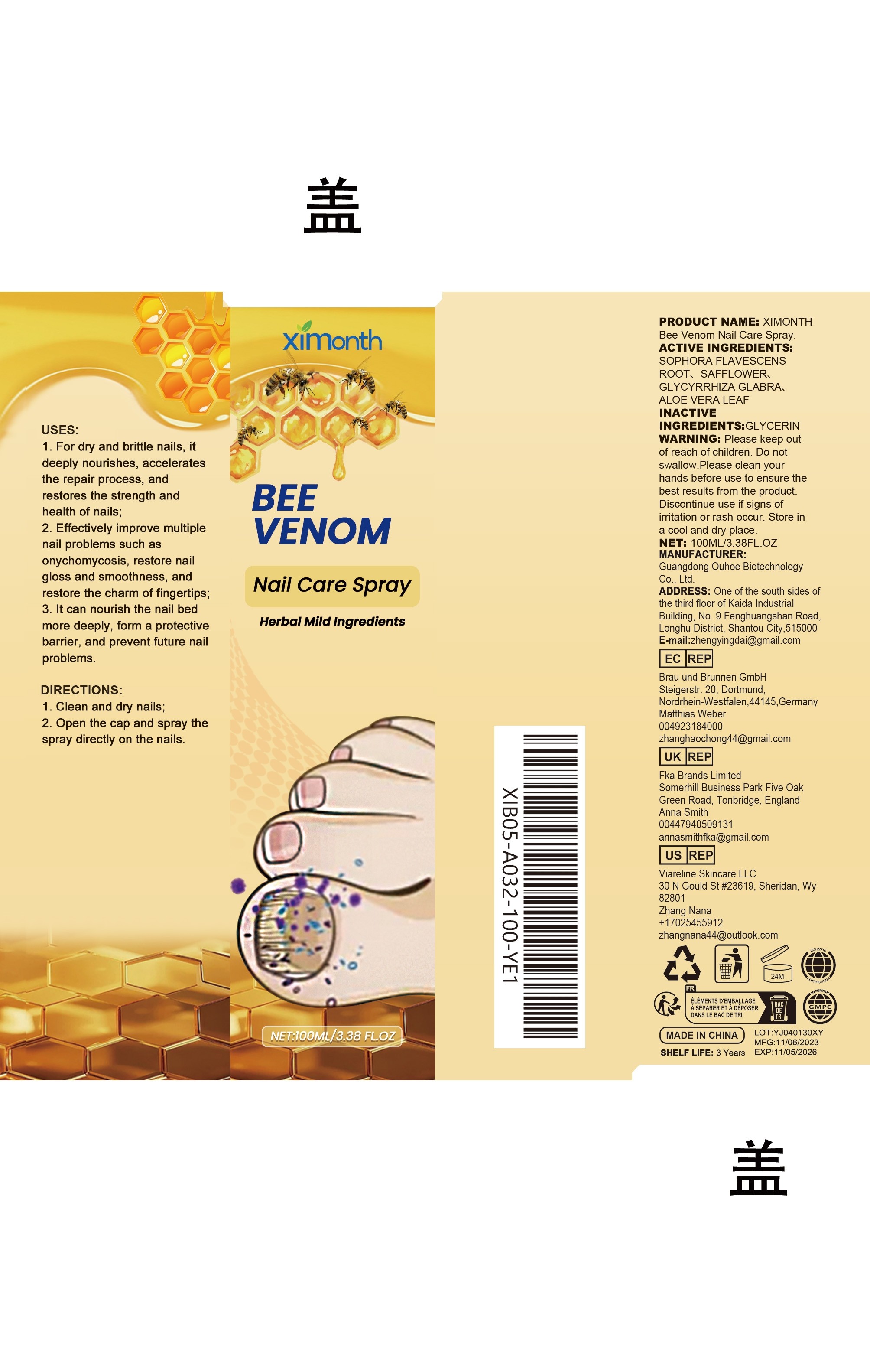 DRUG LABEL: XIMONTH Bee Venom Nail Care
NDC: 84744-006 | Form: SPRAY
Manufacturer: Guangdong Ouhoe Biotechnology Co., Ltd.
Category: otc | Type: HUMAN OTC DRUG LABEL
Date: 20241105

ACTIVE INGREDIENTS: APIS MELLIFERA VENOM 30 mg/100 mg; TOCOPHEROL 15 mg/100 mg; ALOE VERA LEAF 10 mg/100 mg
INACTIVE INGREDIENTS: ALLANTOIN 30 mg/100 mg; WATER 15 mg/100 mg

ACTIVE INGREDIENTS

APIS MELLIFERA VENOM、ALOE VERA LEAF、TOCOPHEROL

PURPOSE

1. For dry and brittle nails, it deeply nourishes, accelerates the repair process, and restores the strength and health of nails;

2. Effectively improve multiple nail problems such as onychomycosis, restore nail gloss and smoothness, and restore the charm of fingertips;

3. It can nourish the nail bed more deeply, form a protective barrier, and prevent future nail problems.

USES

1. Clean and dry nails;

2. Open the cap and spray the spray directly on the nails.

WARNING

Please keep out of reach of children. Do not swallow.Please clean your hands before use to ensure the best results from the product. Discontinue use if signs of irritation or rash occur. Store in a cool and dry place.

STOP USE

Discontinue use if signs of irritation or rash occur.

DO NOT USE

Discontinue use if signs of irritation or rash occur.

KEEP OUT OF REACH OF CHILDREN

Please keep out of reach of children. Do not swallow.

STORAGE AND HANDLING

Store in a cool and dry place.